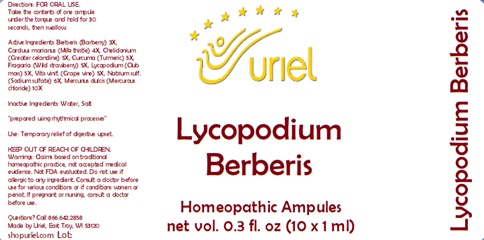 DRUG LABEL: Lycopodium Berberis
NDC: 48951-6048 | Form: LIQUID
Manufacturer: Uriel Pharmacy Inc.
Category: homeopathic | Type: HUMAN OTC DRUG LABEL
Date: 20240112

ACTIVE INGREDIENTS: BERBERIS VULGARIS ROOT BARK 3 [hp_X]/1 mL; MILK THISTLE 4 [hp_X]/1 mL; CHELIDONIUM MAJUS ROOT 5 [hp_X]/1 mL; TURMERIC 5 [hp_X]/1 mL; FRAGARIA VESCA WHOLE 5 [hp_X]/1 mL; LYCOPODIUM CLAVATUM SPORE 5 [hp_X]/1 mL; VITIS VINIFERA LEAF 5 [hp_X]/1 mL; SULFIDE ION 6 [hp_X]/1 mL; CALOMEL 10 [hp_X]/1 mL
INACTIVE INGREDIENTS: WATER; SODIUM CHLORIDE

Lycopodium Berberis

INDICATIONS AND USAGE

Directions: FOR ORAL USE.

DOSAGE AND ADMINISTRATION

Take the contents of one ampule under the tongue and hold for 30 seconds, then swallow.

ACTIVE INGREDIENT

Active Ingredients: Berberis (Barberry) 3X,Carduus marianus (Milk thistle) 4X, Chelidonium (Greater celandine) 5X, Curcuma (Turmeric) 5X, Fragaria (Wild strawberry) 5X, Lycopodium (Club moss) 5X, Vitis vinif. (Grape vine) 5X, Natrium sulf. (Sodium sulfate) 6X, Mercurius dulcis (Mercurous chloride) 10X

Inactive Ingredients: Water, Salt

"prepared using rhythmical processes"

PURPOSE

Use: Temporary relief of digestive upset.

KEEP OUT OF REACH OF CHILDREN.

WARNINGS

Warnings: Claims based on traditional homeopathic practice, not accepted medical evidence. Not FDA evaluated. Do not use if allergic to any ingredient. Consult a doctor before use for serious conditions or if conditions worsen or persist. If pregnant or nursing, consult a doctor before use.

Questions? Call 866.642.2858
Made by Uriel, East Troy, WI 53120
shopuriel.com